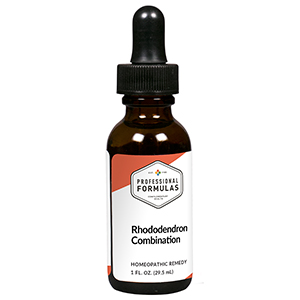 DRUG LABEL: Rhododendron Combination
NDC: 63083-9241 | Form: LIQUID
Manufacturer: Professional Complementary Health Formulas
Category: homeopathic | Type: HUMAN OTC DRUG LABEL
Date: 20190815

ACTIVE INGREDIENTS: BENZOIC ACID 3 [hp_X]/29.5 mL; RHODODENDRON AUREUM LEAF 3 [hp_X]/29.5 mL; FILIPENDULA ULMARIA ROOT 3 [hp_X]/29.5 mL; ACONITUM NAPELLUS WHOLE 4 [hp_X]/29.5 mL; SOLANUM DULCAMARA WHOLE 4 [hp_X]/29.5 mL; RHODODENDRON TOMENTOSUM LEAFY TWIG 4 [hp_X]/29.5 mL; PULSATILLA MONTANA WHOLE 4 [hp_X]/29.5 mL; ASCLEPIAS TUBEROSA FLOWERING TOP 6 [hp_X]/29.5 mL; EUPHORBIA RESINIFERA RESIN 6 [hp_X]/29.5 mL; LITHIUM BENZOATE 10 [hp_X]/29.5 mL
INACTIVE INGREDIENTS: ALCOHOL; WATER

R241

ACTIVE INGREDIENTS

Benzoicum acidum 3X
Rhododendron chrysanthum 3X
Spiraea ulmaria 3X
Aconitum napellus 4X
Dulcamara 4X
Ledum palustre 4X
Pulsatilla 4X
Asclepias tuberosa 6X
Euphorbium officinarum 6X
Lithium benzoicum 10X

QUESTIONS

Professional Formulas

PO Box 2034 Lake Oswego, OR 97035

INDICATIONS

For the temporary relief of minor joint pain, stiffness, or swelling.*

PURPOSE

*Claims based on traditional homeopathic practice, not accepted medical evidence. Not FDA evaluated.

WARNINGS

In case of overdose, get medical help or contact a poison control center right away.

Keep out of the reach of children.

PREGNANCY OR BREAST FEEDING

If pregnant or breastfeeding, ask a healthcare professional before use.

DIRECTIONS

Place drops under tongue 30 minutes before/after meals. Adults and children 12 years and over: Take 10 drops up to 3 times per day. Consult a physician for use in children under 12 years of age.

OTHER INFORMATION

Tamper resistant. If seal is broken, do not use. After opening, close container tightly and store at room temperature away from heat.

INACTIVE INGREDIENTS

40% ethanol, purified water.

LABEL

Est 1985

Professional Formulas

Complementary Health

Rhododendron Combination

Homeopathic Remedy

1 FL. OZ. (29.5 mL)